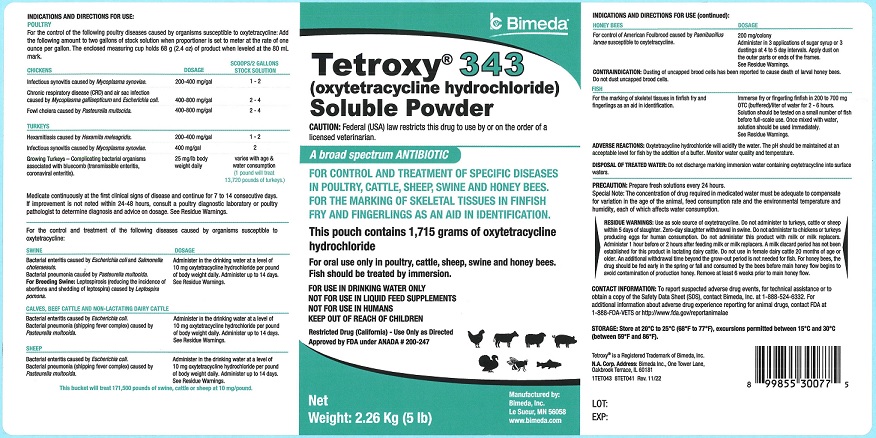 DRUG LABEL: Tetroxy 343
NDC: 61133-3401 | Form: POWDER
Manufacturer: Bimeda, Inc.
Category: animal | Type: PRESCRIPTION ANIMAL DRUG LABEL
Date: 20240328

ACTIVE INGREDIENTS: OXYTETRACYCLINE HYDROCHLORIDE 102.4 g/135.5 g

DESCRIPTION

Tetroxy® 343
(oxytetracycline hydrochloride)
Soluble Powder

CAUTION: Federal (USA) law restricts this drug to use by or on the order of a licensed veterinarian.

A broad spectrum ANTIBIOTIC

FOR CONTROL AND TREATMENT OF SPECIFIC DISEASES IN POULTRY, CATTLE, SHEEP, SWINE AND HONEY BEES.
FOR THE MARKING OF SKELETAL TISSUES IN FINFISH FRY AND FINGERLINGS AS AN AID IN IDENTIFICATION.

This pouch contains 1,715 grams of oxytetracycline hydrochloride.

For oral use only in poultry, cattle, sheep, swine and honey bees.
Fish should be treated by immersion.

FOR USE IN DRINKING WATER ONLY
NOT FOR USE IN LIQUID FEED SUPPLEMENTS
NOT FOR USE IN HUMANS
KEEP OUT OF REACH OF CHILDREN

Restricted Drug (California) - Use Only as Directed

Approved by FDA under ANADA # 200-247

INDICATIONS AND DIRECTIONS FOR USE:

POULTRY

For the control of the following poultry diseases caused by organisms susceptible to oxytetracycline: Add the following amount to two gallons of stock solution when proportioner is set to meter at the rate of one ounce per gallon. The enclosed measuring cup holds 68 g (2.4 oz) of product when leveled at the 80 mL mark.

CHICKENS | DOSAGE | SCOOPS/2 GALLONS STOCK SOLUTION
Infectious synovitis caused by Mycoplasma synoviae. | 200-400 mg/gal | 1-2
Chronic respiratory disease (CRD) and air sac infection caused by Mycoplasma gallisepticum and Escherichia coli. | 400-800 mg/gal | 2-4
Fowl cholera caused by Pasteurella multocida. | 400-800 mg/gal | 2-4
TURKEYS
Hexamitiasis caused by Hexamita meleagridis. | 200-400 mg/gal | 1-2
Infectious synovitis caused by Mycoplasma synoviae. | 400 mg/gal | 2
Growing Turkeys-Complicating bacterial organisms associated with bluecomb (transmissible enteritis, coronaviral enteritis). | 25 mg/lb body weight daily | varies with age & water consumption (1 pound will treat 13,720 pounds of turkeys.)

INDICATIONS AND USAGE

Medicate continuously at the first clinical signs of disease and continue for 7 to 14 consecutive days. If improvement is not noted within 24-48 hours, consult a poultry diagnostic laboratory or poultry pathologist to determine diagnosis and advice on dosage. See Residue Warnings.

For the control and treatment of the following diseases caused by organisms susceptible to oxytetracycline:

SWINE | DOSAGE
Bacterial enteritis caused by Escherichia coli and Salmonella choleraesuis. Bacterial pneumonia caused by Pasteurella multocida. For Breeding Swine: Leptospirosis (reducing the incidence of abortions and shedding of leptospira) caused by Leptospira pomona. | Administer in the drinking water at a level of 10 mg oxytetracycline hydrochloride per pound of body weight daily. Administer up to 14 days. See Residue Warnings.
CALVES, BEEF CATTLE AND NON-LACTATING CATTLE | DOSAGE
Bacterial enteritis caused by Escherichia coli. Bacterial pneumonia (shipping fever complex) caused by Pasteurella multocida. | Administer in the drinking water at a level of 10 mg oxytetracycline hydrochloride per pound of body weight daily. Administer up to 14 days. See Residue Warnings.
SHEEP | DOSAGE
Bacterial enteritis caused by Escherichia coli. Bacterial pneumonia (shipping fever complex) caused by Pasteurella multocida. | Administer in the drinking water at a level of 10 mg oxytetracycline hydrochloride per pound of body weight daily. Administer up to 14 days. See Residue Warnings.
This bucket will treat 171,500 pounds of swine, cattle or sheep at 10 mg/pound.
HONEY BEES | DOSAGE
For control of American Foulbrood caused by Paenibacillus larvae susceptible to oxytetracycline. | 200 mg/colony; Administer in 3 applications of sugar syrup or 3 dustings at 4 to 5 day intervals. Apply dust on the outer parts or ends of the frames. See Residue Warnings.
CONTRAINDICATION: Dusting of uncapped brood cells has been reported to cause death of larval honey bees. Do not dust uncapped brood cells.
FISH | DOSAGE
For the marking of skeletal tissues in finfish fry and fingerlings as an aid in identification. | Immerse fry or fingerling finfish in 200 to 700 mg OTC (buffered)/liter of water for 2-6 hours. Solution should be tested on a small number of fish before full-scale use. Once mixed with water, solution should be used immediately. See Residue Warnings.

ADVERSE REACTIONS

ADVERSE REACTIONS: Oxytetracycline hydrochloride will acidify the water. The pH should be maintained at an acceptable level for fish by the addition of a buffer. Monitor water quality and temperature.

DISPOSAL OF TREATED WATER: Do not discharge marking immersion water containing oxytetracycline into surface waters.

PRECAUTIONS

PRECAUTION: Prepare fresh solutions every 24 hours.

Special Note: The concentration of drug required in medicated water must be adequate to compensate for variation in the age of the animal, feed consumption rate and the environmental temperature and humidity, each of which affects water consumption.

RESIDUE WARNING

RESIDUE WARNINGS: Use as sole source of oxytetracycline. Do not administer to turkeys, cattle or sheep within 5 days of slaughter. Zero-day slaughter withdrawal in swine. Do not administer to chickens or turkeys producing eggs for human consumption. Do not administer this product with milk or milk replacers. Administer 1 hour before or 2 hours after feeding milk or milk replacers. A milk discard period has not been established for this product in lactating dairy cattle. Do not use in female dairy cattle 20 months of age or older. An additional withdrawal time beyond the grow-out period is not needed for fish. For honey bees, the drug should be fed early in the spring or fall and consumed by the bees before main honey flow begins to avoid contamination of production honey. Remove at least 6 weeks prior to main honey flow.

CONTACT INFORMATION: To report suspected adverse drug events, for technical assistance or to obtain a copy of the Safety Data Sheet (SDS), contact Bimeda, Inc. at 1-888-524-6332. For additional information about adverse drug experience reporting for animal drugs, contact FDA at 1-888-FDA-VETS or http://www.fda.gov/reportanimalae

STORAGE AND HANDLING

STORAGE: Store at 20°C to 25°C (68°F to 77°F), excursions permitted between 15°C and 30°C (between 59°F and 86°F).